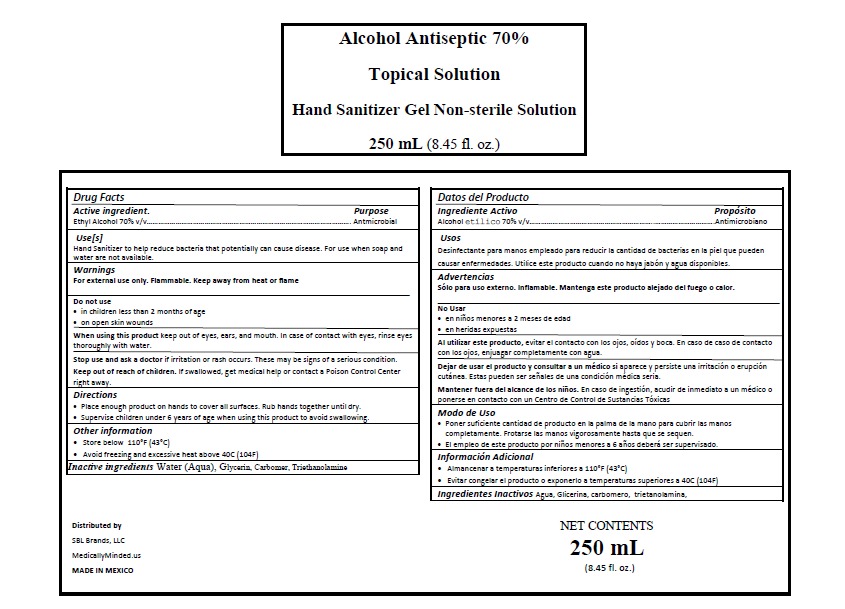 DRUG LABEL: HAND SANITIZER
NDC: 77196-003 | Form: GEL
Manufacturer: Ignacio Reyes González
Category: otc | Type: HUMAN OTC DRUG LABEL
Date: 20200522

ACTIVE INGREDIENTS: ALCOHOL 0.7 mL/1 mL
INACTIVE INGREDIENTS: TRIETHANOLAMINE CAPROYL GLUTAMATE 0.002 mL/1 mL; GLYCERIN 0.0375 mL/1 mL; WATER 0.2585 mL/1 mL; CARBOMER 940 0.002 mL/1 mL

HAND SANITIZER GEL 250 mL

DIRECTIONS OF DOSAGE AND ADMINISTRATION

Directions

Place enough product on hands to cover all surfaces. Rub hands together until dry.

Supervise children under 6 years of age when using this product to avoid swallowing.

INACTIVE INGREDIENTS

Water, Glycerin, Carbomer, Triethanolamine

INDICATIONS AND USAGE

Place enough product on hands to cover all surfaces. Rub hands together until dry.

Supervise children under 6 years of age when using this product to avoid swallowing.

Keep out of reach of children. If swallowed, get medical help or contact a Poison Control Center right away.

ANTIMICROBIAL

WARNINGS

For external use only. Flammable. Keep away from heat or flame

When using this product keep out of eyes, ears, and mouth. In case of contact with eyes, rinse eyes thoroughly with water.

Stop use and ask a doctor if irritation or rash occurs. These may be signs of a serious condition.

ACTIVE INGREDIENT

Ethyl Alcohol 70%